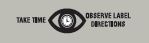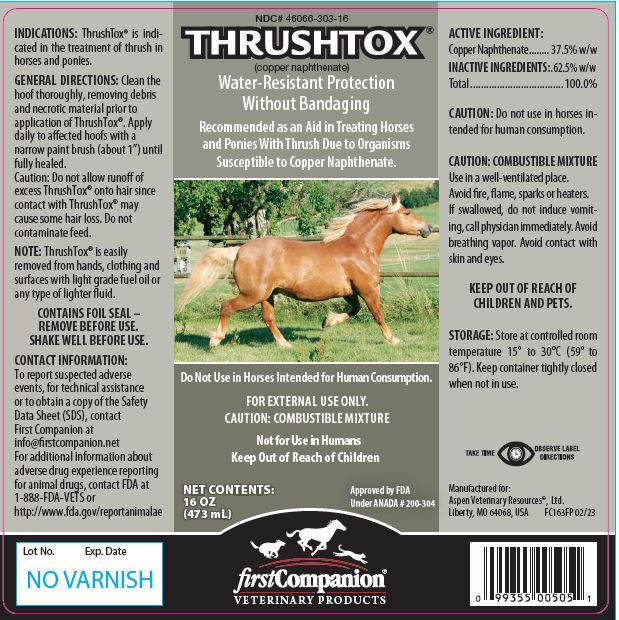 DRUG LABEL: THRUSHTOX
NDC: 46066-303 | Form: LIQUID
Manufacturer: Aspen Veterinary Resources
Category: animal | Type: OTC ANIMAL DRUG LABEL
Date: 20231009

ACTIVE INGREDIENTS: COPPER NAPHTHENATE 0.825 g/1 mL

ThrushTox®

INFORMATION FOR OWNERS/CAREGIVERS

(copper naphthenate)

Water-Resistant Protection Without Bandaging

Recommended as an Aid in Treating Horses and Ponies With Thrush Due to Organisms Susceptible to Copper Naphthenate.

Do Not Use in Horses Intended for Human Consumption.

FOR EXTERNAL USE ONLY.
CAUTION: COMBUSTIBLE MIXTURE

Not for Use in Humans
Keep Out of Reach of Children

INDICATIONS:

ThrushTox® is indicated in the treatment of thrush in horses and ponies.

GENERAL DIRECTIONS:

Clean the hoof thoroughly, removing debris and necrotic material prior to application of ThrushTox®. Apply daily to affected hoofs with a narrow paint brush (about 1”) until fully healed. Caution: Do not allow runoff of excess ThrushTox® onto hair since contact with ThrushTox® may cause some hair loss. Do not contaminate feed.

INFORMATION FOR OWNERS/CAREGIVERS

NOTE: ThrushTox® is easily removed from hands, clothing and surfaces with light grade fuel oil or any type of lighter fluid.

CONTAINS FOIL SEAL – REMOVE BEFORE USE.

SHAKE WELL BEFORE USE.

CONTACT INFORMATION:

To report suspected adverse events, for technical assistance or to obtain a copy of the Safety Data Sheet (SDS), contact First Companion at info@firstcompanion

For additional information about adverse drug experience reporting for animal drugs, contact FDA at 1-888-FDA-VETS or http://www.fda.gov/reportanimalae

ACTIVE INGREDIENT:

Copper Naphthenate........ 37.5% w/w

INACTIVE INGREDIENTS:

.62.5% w/w
Total...................................100.0%

CAUTION:

Do not use in horses intended for human consumption.

CAUTION: COMBUSTIBLE MIXTURE.

Use in a well-ventilated place.

Avoid fire, flame, sparks or heaters.

If swallowed, do not induce vomiting, call physician immediately. Avoid breathing vapor. Avoid contact with skin and eyes.

KEEP OUT OF REACH OF CHILDREN AND PETS.

STORAGE:

Store at controlled room temperature 15º to 30ºC (59º to 86ºF). Keep container tightly closed when not in use.

NET CONTENTS:

16 OZ (473 mL)

Approved by FDA Under ANADA # 200-304

INFORMATION FOR OWNERS/CAREGIVERS

Manufactured for:
Aspen Veterinary Resources®, Ltd.
Liberty, MO 64068, USA FC163FP 02/23